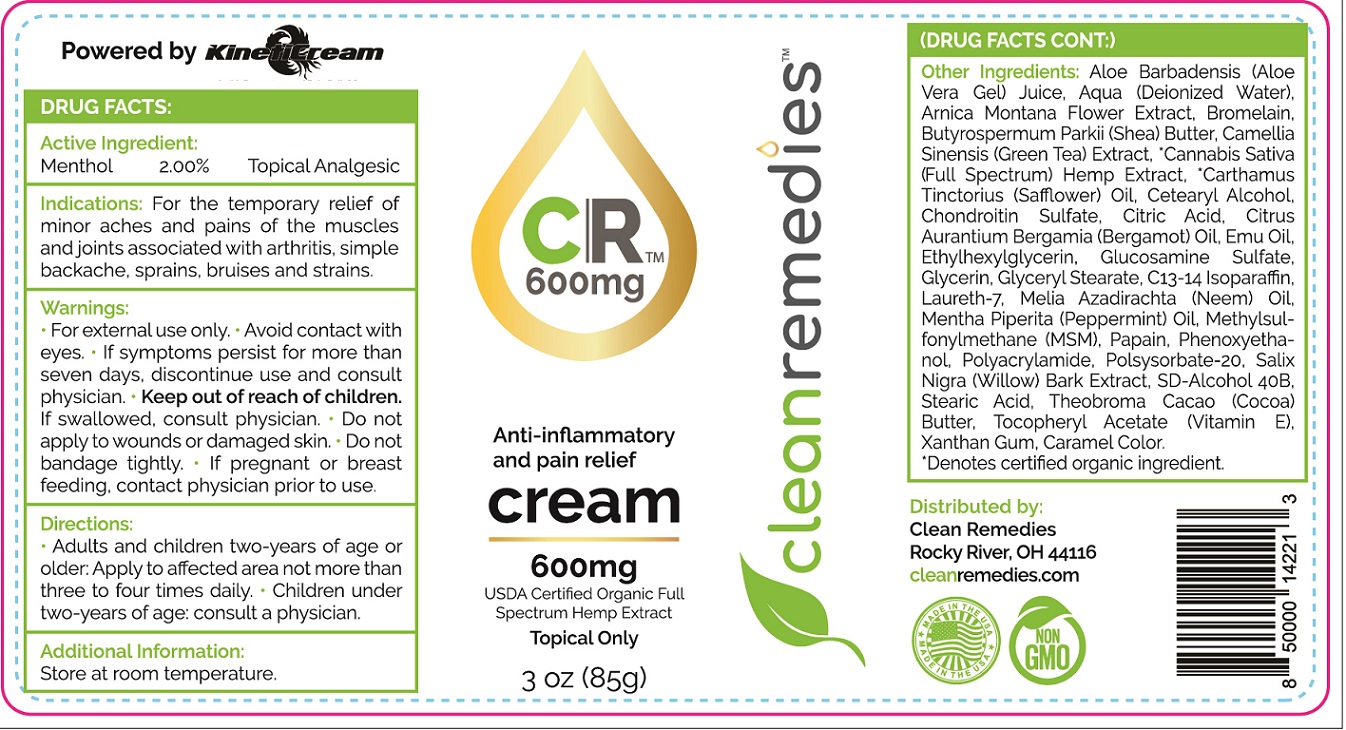 DRUG LABEL: CLEAN REMEDIES CR PAIN RELIEF
NDC: 73371-048 | Form: CREAM
Manufacturer: Clean Remedies, LLC
Category: otc | Type: HUMAN OTC DRUG LABEL
Date: 20231111

ACTIVE INGREDIENTS: MENTHOL 20 mg/1 g
INACTIVE INGREDIENTS: ALOE VERA LEAF; WATER; ARNICA MONTANA FLOWER; BROMELAINS; SHEA BUTTER; GREEN TEA LEAF; SAFFLOWER; CETOSTEARYL ALCOHOL; CITRIC ACID MONOHYDRATE; BERGAMOT OIL; EMU OIL; ETHYLHEXYLGLYCERIN; GLUCOSAMINE SULFATE; GLYCERIN; GLYCERYL MONOSTEARATE; C13-14 ISOPARAFFIN; LAURETH-7; PEPPERMINT; DIMETHYL SULFONE; PAPAIN; PHENOXYETHANOL; POLYSORBATE 20; SALIX NIGRA BARK; STEARIC ACID; COCOA; .ALPHA.-TOCOPHEROL ACETATE; XANTHAN GUM; CARAMEL

CLEAN REMEDIES CR PAIN RELIEF CREAM

Active Ingredient:

Menthol 2.00%

PURPOSE

Topical Analgesic

Indications:

For the temporary relief of minor aches and pains of the muscles and joints associated with arthritis, simple backache, sprains, bruises and strains.

Warnings:

For external use only. Avoid contact with eyes. If symptoms persist for more than seven days, discontinue use and consult physician.

Keep out of reach of children.

If swallowed, consult physician.

Do not apply

to wounds or damaged skin. Do not bandage tightly.

If pregnant or breast feeding,

contact physician prior to use.

Directions:

- Adults and children two-years of age or older: Apply to affected area not more than three to four times daily.
- Children under two-years of age: consult a physician.

Additional Information:

Store at room temperature.

Other Ingredients:

Aloe Barbadensis (Aloe Vera Gel) Juice, Aqua (Deionized Water), Arnica Montana Flower Extract, Bromelain, Butyrospermum Parkii (Shea) Butter, Camellia Sinensis (Green Tea) Extract, Cannabis Sativa (Full Spectrum) Hemp Extract, Carthamus Tinctorius (Safflower) Oil, Cetearyl Alcohol, Chondroitin Sulfate, Citric Acid, Citrus Aurantium Bergamia (Bergamot) Oil, Emu Oil, Ethylhexylglycerin, Glucosamine Sulfate, Glycerin, Glyceryl Stearate, C13-14 Isoparaffin, Laureth-7, Melia Azadirachta (Neem) Oil, Mentha Piperita (Peppermint) Oil, Methylsulfonylmethane (MSM) Papain, Phenoxyethanol, Polyacrylamide, Polysorbate-20, Salix Nigra (Willow) Bark Extract, SD-Alcohol 40B, Stearic Acid, Theobroma Cacao (Cocoa) Butter, Tocopheryl Acetate (Vitamin E), Xanthan Gum, Caramel Color. *Denotes cerified organic ingredient.